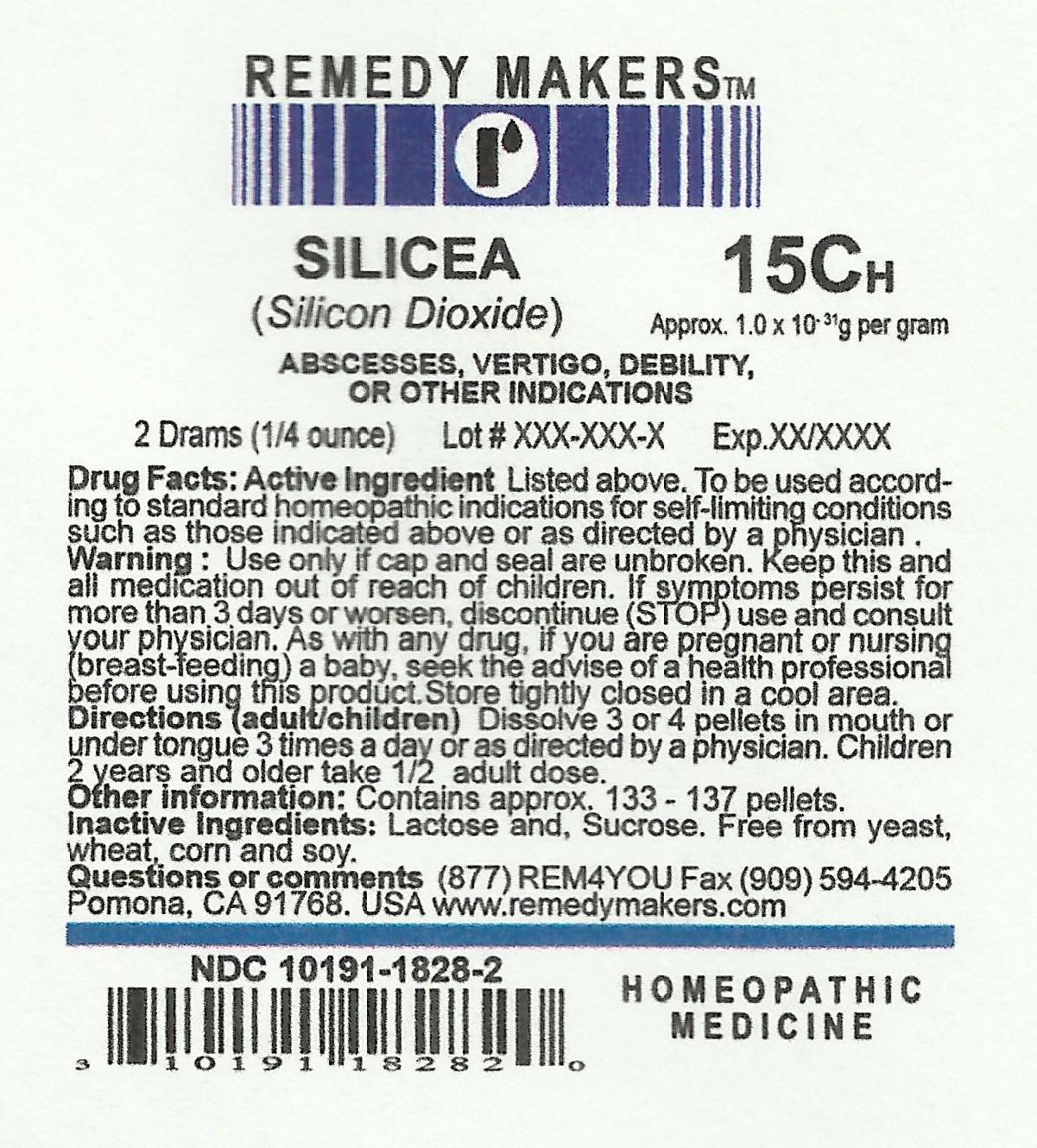 DRUG LABEL: SILICEA
NDC: 10191-1828 | Form: PELLET
Manufacturer: REMEDY MAKERS
Category: homeopathic | Type: HUMAN OTC DRUG LABEL
Date: 20111230

ACTIVE INGREDIENTS: SILICON DIOXIDE 15 [hp_C]/1 1
INACTIVE INGREDIENTS: SUCROSE; LACTOSE

SILICEA 15C (Silicon Dioxide)

PURPOSE

ABSCESSES, VERTIGO, DEBILITY, OR OTHER INDICATIONS

ACTIVE INGREDIENT

SILICON DIOXIDE

KEEP OUT OF REACH OF CHILDREN

WARNING:Keep this and all medications out of reach of children.

INDICATIONS AND USAGE

INDICATIONS: To be use according to standard homeopathic indications, for self-limiting conditions such as these indicated above or as directed by a physician.

WARNINGS

WARNING: Use only if cap and seal are unbroken. If symptoms persist for more than 3 days or worsen, discontinue (STOP) use and consult your physician. As with any drug. If you are pregnant or nursing (breast-feeding) a baby, seek the advise of a health professional before using this product. Store tightly closed in a cool area.

DOSAGE AND ADMINISTRATION

Directions:(adult/children) Dissolve 3 or 4 pellets in mouth or under tongue 3 times a day or as directed by a physician. Children 2 years and older take 1/2 the adult dose.

Inactive Ingredient: Lactose and Sucrose. Free from yeast, wheat, corn and soy.

Questions or comments.(877)REM4YOU. Fax (909)594-4205 Pomona, CA. 91768. USA www.remedymakers.com

Other information: Contain approx.133 - 137 pellets.